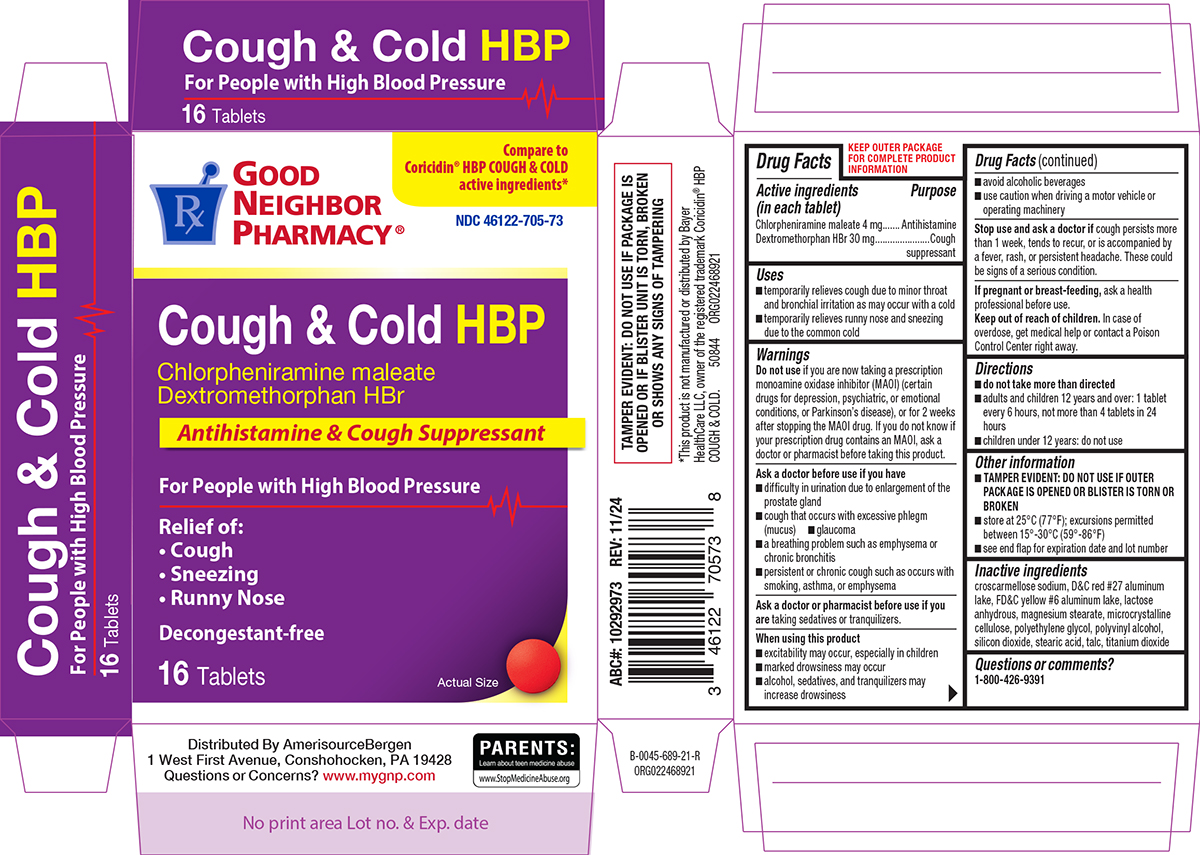 DRUG LABEL: Cough and Cold HBP
NDC: 46122-705 | Form: TABLET, FILM COATED
Manufacturer: Amerisource Bergen
Category: otc | Type: HUMAN OTC DRUG LABEL
Date: 20260120

ACTIVE INGREDIENTS: CHLORPHENIRAMINE MALEATE 4 mg/1 1; DEXTROMETHORPHAN HYDROBROMIDE 30 mg/1 1
INACTIVE INGREDIENTS: CROSCARMELLOSE SODIUM; D&C RED NO. 27 ALUMINUM LAKE; FD&C YELLOW NO. 6 ALUMINUM LAKE; ANHYDROUS LACTOSE; MAGNESIUM STEARATE; MICROCRYSTALLINE CELLULOSE; POLYETHYLENE GLYCOL, UNSPECIFIED; POLYVINYL ALCOHOL, UNSPECIFIED; SILICON DIOXIDE; STEARIC ACID; TALC; TITANIUM DIOXIDE

Good Neighbor Pharmacy 44-689

Active ingredients (in each tablet)

Chlorpheniramine maleate 4 mg
Dextromethorphan HBr 30 mg

Purpose

Antihistamine
Cough suppressant

Uses

- temporarily relieves cough due to minor throat and bronchial irritation as may occur with a cold
- temporarily relieves runny nose and sneezing due to the common cold

Warnings

Do not use

if you are now taking a prescription monoamine oxidase inhibitor (MAOI) (certain drugs for depression, psychiatric, or emotional conditions, or Parkinson’s disease), or for 2 weeks after stopping the MAOI drug. If you do not know if your prescription drug contains an MAOI, ask a doctor or pharmacist before taking this product.

Ask a doctor before use if you have

- difficulty in urination due to enlargement of the prostate gland
- cough that occurs with excessive phlegm (mucus)
- glaucoma
- a breathing problem such as emphysema or chronic bronchitis
- persistent or chronic cough such as occurs with smoking, asthma, or emphysema

Ask a doctor or pharmacist before use if you are

taking sedatives or tranquilizers.

When using this product

- excitability may occur, especially in children
- marked drowsiness may occur
- alcohol, sedatives, and tranquilizers may increase drowsiness
- avoid alcoholic beverages
- use caution when driving a motor vehicle or operating machinery

Stop use and ask a doctor if

cough persists more than 1 week, tends to recur, or is accompanied by a fever, rash, or persistent headache. These could be signs of a serious condition.

If pregnant or breast-feeding,

ask a health professional before use.

Keep out of reach of children.

In case of overdose, get medical help or contact a Poison Control Center right away.

Directions

- do not take more than directed
- adults and children 12 years and over: 1 tablet every 6 hours, not more than 4 tablets in 24 hours
- children under 12 years: do not use

Other information

- TAMPER EVIDENT: DO NOT USE IF OUTER PACKAGE IS OPENED OR BLISTER IS TORN OR BROKEN
- store at 25°C (77°F); excursions permitted between 15°-30°C (59°-86°F)
- see end flap for expiration date and lot number

Inactive ingredients

croscarmellose sodium, D&C red #27 aluminum lake, FD&C yellow #6 aluminum lake, lactose anhydrous, magnesium stearate, microcrystalline cellulose, polyethylene glycol, polyvinyl alcohol, silicon dioxide, stearic acid, talc, titanium dioxide

Questions or comments?

1-800-426-9391

Principal display panel

Good
Neighbor
Pharmacy®

Compare to
Coricidin® HBP COUGH & COLD
active ingredients*

NDC 46122-705-73

Cough & Cold HBP

Chlorpheniramine maleate
Dextromethorphan HBr

Antihistamine & Cough Suppressant

For People with High Blood Pressure

Relief of:
• Cough
• Sneezing
• Runny Nose

Decongestant-free

16 Tablets

Actual Size

TAMPER EVIDENT: DO NOT USE IF PACKAGE IS
OPENED OR IF BLISTER UNIT IS TORN, BROKEN
OR SHOWS ANY SIGNS OF TAMPERING

PARENTS:
Learn about teen medicine abuse
www.StopMedicineAbuse.org

*This product is not manufactured or distributed by Bayer
HealthCare LLC, owner of the registered trademark Coricidin® HBP
COUGH & COLD. 50844 ORG022468921

Distributed By AmerisourceBergen
1 West First Avenue, Conshohocken, PA 19428
Questions or Concerns? www.mygnp.com

GNP 44-689